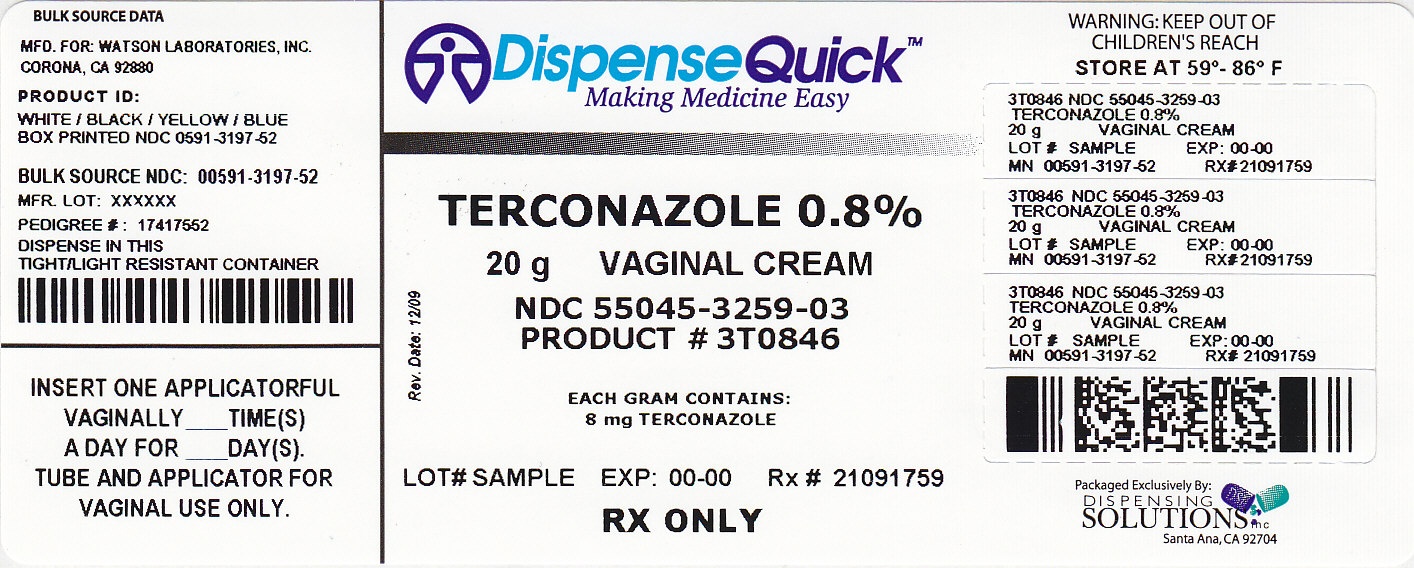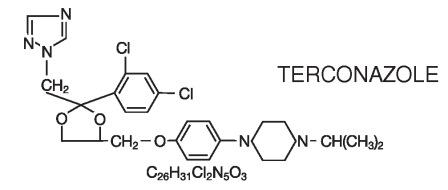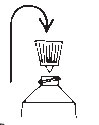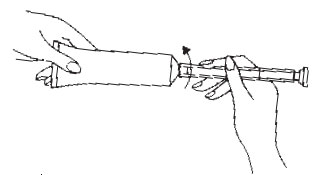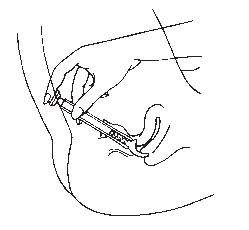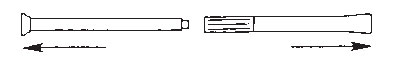 DRUG LABEL: TERCONAZOLE
NDC: 55045-3259 | Form: CREAM
Manufacturer: Dispensing Solutions, Inc.
Category: prescription | Type: HUMAN PRESCRIPTION DRUG LABEL
Date: 20110922

ACTIVE INGREDIENTS: TERCONAZOLE 8 mg/1 g
INACTIVE INGREDIENTS: BUTYLATED HYDROXYANISOLE; CETYL ALCOHOL; ISOPROPYL MYRISTATE; POLYSORBATE 60; POLYSORBATE 80; PROPYLENE GLYCOL; STEARYL ALCOHOL; WATER

TERCONAZOLE VAGINAL CREAM 0.4%
7-Day Regimen
TERCONAZOLE VAGINAL CREAM 0.8%
3-Day Regimen

description

Terconazole Vaginal Cream 0.4% is a white to off-white, water washable cream for intravaginal administration containing 0.4% of the antifungal agent terconazole, cis-1-[p-[[2-(2,4-Dichlorophenyl)-2-(1H-1,2,4-triazol-1-ylmethyl)-1,3-dioxolan-4-yl]methoxy]phenyl]-4-isopropylpiperazine, compounded in a cream base consisting of butylated hydroxyanisole, cetyl alcohol, isopropyl myristate, polysorbate 60, polysorbate 80, propylene glycol, stearyl alcohol, and purified water.

Terconazole Vaginal Cream 0.8% is a white to off-white, water washable cream for intravaginal administration containing 0.8% of the antifungal agent terconazole, cis-1-[p-[[2-(2,4-Dichlorophenyl)-2-(1H-1,2,4-triazol-1-ylmethyl)-1,3-dioxolan-4-yl]methoxy]phenyl]-4-isopropylpiperazine, compounded in a cream base consisting of butylated hydroxyanisole, cetyl alcohol, isopropyl myristate, polysorbate 60, polysorbate 80, propylene glycol, stearyl alcohol, and purified water.

The structural formula of terconazole is as follows:

Terconazole, a triazole derivative, is a white to almost white powder with a molecular weight of 532.47. It is insoluble in water; sparingly soluble in ethanol; and soluble in butanol.

clinical pharmacology

Following intravaginal administration of terconazole in humans, absorption ranged from 5–8% in three hysterectomized subjects and 12–16% in two non-hysterectomized subjects with tubal ligations.

Following daily intravaginal administration of 0.8% terconazole 40 mg (0.8% cream x 5 g) for seven days to normal humans, plasma concentrations were low and gradually rose to a daily peak (mean of 5.9 ng/mL or 0.006 mcg/mL) at 6.6 hours.

Results from similar studies in patients with vulvovaginal candidiasis indicate that the slow rate of absorption, the lack of accumulation, and the mean peak plasma concentration of terconazole was not different from that observed in healthy women. The absorption characteristics of terconazole 0.8% in pregnant or non-pregnant patients with vulvovaginal candidiasis were also similar to those found in normal volunteers.

Following oral (30 mg) administration of ^14C-labelled terconazole, the harmonic half-life of elimination from the blood for the parent terconazole was 6.9 hours (range 4.0–11.3). Terconazole is extensively metabolized; the plasma AUC for terconazole compared to the AUC for total radioactivity was 0.6%. Total radioactivity was eliminated from the blood with a harmonic half-life of 52.2 hours (range 44–60). Excretion of radioactivity was both by renal (32–56%) and fecal (47–52%) routes.

In vitro, terconazole is highly protein bound (94.9%) and the degree of binding is independent of drug concentration.

Photosensitivity reactions were observed in some normal volunteers following repeated dermal application of terconazole 2.0% and 0.8% creams under conditions of filtered artificial ultraviolet light.

Photosensitivity reactions have not been observed in U.S. and foreign clinical trials in patients who were treated with terconazole suppositories or vaginal cream (0.4% and 0.8%).

Microbiology:

Terconazole exhibits fungicidal activity in vitro against Candida albicans. Antifungal activity has also been demonstrated against other fungi. The MIC values of terconazole against most Lactobacillus spp. typically found in the human vagina were ≥128 mcg/mL; therefore these beneficial bacteria were not affected by drug treatment.

The exact pharmacologic mode of action of terconazole is uncertain; however, it may exert its antifungal activity by the disruption of normal fungal cell membrane permeability. No resistance to terconazole has developed during successive passages of C. albicans.

indications and usage

Terconazole Vaginal Cream is indicated for the local treatment of vulvovaginal candidiasis (moniliasis). As this product is effective only for vulvovaginitis caused by the genus Candida, the diagnosis should be confirmed by KOH smears and/or cultures.

contraindications

Patients known to be hypersensitive to terconazole or to any of the components of the cream.

warnings

None.

precautions

General:

Discontinue use and do not retreat with terconazole if sensitization, irritation, fever, chills or flu-like symptoms are reported during use.

Laboratory Tests:

If there is lack of response to terconazole, appropriate microbiologic studies (standard KOH smear and/or cultures) should be repeated to confirm the diagnosis and rule out other pathogens.

Drug Interactions:

PRECAUTIONS

Terconazole Vaginal Cream 0.4%:
The therapeutic effect of this product is not affected by oral contraceptive usage.

PRECAUTIONS

Terconazole Vaginal Cream 0.8%:
The levels of estradiol (E2) and progesterone did not differ significantly when 0.8% terconazole vaginal cream was administered to healthy female volunteers established on a low dose oral contraceptive.

Carcinogenesis, Mutagenesis, Impairment of Fertility:

Carcinogenesis:
Studies to determine the carcinogenic potential of terconazole have not been performed.

CARCINOGENESIS AND MUTAGENESIS AND IMPAIRMENT OF FERTILITY

Mutagenicity:
Terconazole was not mutagenic when tested in vitro for induction of microbial point mutations (Ames test), or for inducing cellular transformation, or in vivo for chromosome breaks (micronucleus test) or dominant lethal mutations in mouse germ cells.

Impairment of Fertility:
No impairment of fertility occurred when female rats were administered terconazole orally up to 40 mg/kg/day for a three month period.

Pregnancy: Teratogenic Effects:

Teratogenic Effects

Pregnancy Category C.

There was no evidence of teratogenicity when terconazole was administered orally up to 40 mg/kg/day (50x the recommended intravaginal human dose of the 0.8% vaginal cream formulation, and 100x the intravaginal human dose of the 0.4% vaginal cream formulation) in rats, or 20 mg/kg/day in rabbits, or subcutaneously up to 20 mg/kg/day in rats.

Dosages at or below 10 mg/kg/day produced no embryotoxicity; however, there was a delay in fetal ossification at 10 mg/kg/day in rats. There was some evidence of embryotoxicity in rabbits and rats at 20-40 mg/kg. In rats, this was reflected as a decrease in litter size and number of viable young and reduced fetal weight. There was also delay in ossification and an increased incidence of skeletal variants.

The no-effect dose of 10 mg/kg/day resulted in a mean peak plasma level of terconazole in pregnant rats of 0.176 mcg/mL which exceeds by 44 times the mean peak plasma level (0.004 mcg/mL) seen in normal subjects after intravaginal administration of terconazole 0.4% vaginal cream, and by 30 times the mean peak plasma level (0.006 mcg/mL) seen in normal subjects after intravaginal administration of terconazole 0.8% vaginal cream. This safety assessment does not account for possible exposure of the fetus through direct transfer to terconazole from the irritated vagina by diffusion across amniotic membranes.

Since terconazole is absorbed from the human vagina, it should not be used in the first trimester of pregnancy unless the physician considers it essential to the welfare of the patient.

Nursing Mothers:

It is not known whether this drug is excreted in human milk. Animal studies have shown that rat offspring exposed via the milk of treated (40 mg/kg/orally) dams showed decreased survival during the first few post-partum days, but overall pup weight and weight gain were comparable to or greater than controls throughout lactation. Because many drugs are excreted in human milk, and because of the potential for adverse reaction in nursing infants from terconazole, a decision should be made whether to discontinue nursing or to discontinue the drug, taking into account the importance of the drug to the mother.

Pediatric Use:

Safety and efficacy in children have not been established.

Geriatric Use:

Clinical studies of terconazole did not include sufficient numbers of subjects aged 65 and over to determine whether they respond differently from younger subjects. Other reported clinical experience has not identified differences in responses between the elderly and younger patients.

adverse reactions

Terconazole Vaginal Cream 0.4%:

During controlled clinical studies conducted in the United States, 521 patients with vulvovaginal candidiasis were treated with terconazole 0.4% vaginal cream. Based on comparative analyses with placebo, the adverse experiences considered most likely related to terconazole 0.4% vaginal cream were headache (26% vs. 17% with placebo) and body pain (2.1% vs. 0% with placebo). Vulvovaginal burning (5.2%), itching (2.3%) or irritation (3.1%) occurred less frequently with terconazole 0.4% vaginal cream than with the vehicle placebo. Fever (1.7% vs. 0.5% with placebo) and chills (0.4% vs. 0.0% with placebo) have also been reported. The therapy-related dropout rate was 1.9%. The adverse drug experience on terconazole most frequently causing discontinuation was vulvovaginal itching (0.6%), which was lower than the incidence for placebo (0.9%).

Terconazole Vaginal Cream 0.8%:

During controlled clinical studies conducted in the United States, patients with vulvovaginal candidiasis were treated with terconazole 0.8% vaginal cream for three days. Based on comparative analyses with placebo and a standard agent, the adverse experiences considered most likely related to terconazole 0.8% vaginal cream were headache (21% vs. 16% with placebo) and dysmenorrhea (6% vs. 2% with placebo). Genital complaints in general, and burning and itching in particular, occurred less frequently in the terconazole 0.8% vaginal cream 3 day regimen (5% vs. 6%–9% with placebo). Other adverse experiences reported with terconazole 0.8% vaginal cream were abdominal pain (3.4% vs. 1% with placebo) and fever (1% vs. 0.3% with placebo). The therapy-related dropout rate was 2.0% for the terconazole 0.8% vaginal cream. The adverse drug experience most frequently causing discontinuation of therapy was vulvovaginal itching, 0.7% with the terconazole 0.8% vaginal cream group and 0.3% with the placebo group.

overdosage

Overdose of terconazole in humans has not been reported to date. In the rat, the oral LD 50 values were found to be 1741 and 849 mg/kg for the male and female, respectively. The oral LD 50 values for the male and female dog were ≅1280 and ≥640 mg/kg, respectively.

dosage and administration

Terconazole Vaginal Cream 0.4%:

One full applicator (5 g) of Terconazole Vaginal Cream (20 mg terconazole) should be administered intravaginally once daily at bedtime for seven consecutive days.

Terconazole Vaginal Cream 0.8%:

One full applicator (5 g) of Terconazole Vaginal Cream (40 mg terconazole) should be administered intravaginally once daily at bedtime for three consecutive days.

Before prescribing another course of therapy, the diagnosis should be reconfirmed by smears and/or cultures and other pathogens commonly associated with vulvovaginitis ruled out. The therapeutic effect of these products is not affected by menstruation.

how supplied

Terconazole Vaginal Cream 0.4% is available in 45 g (NDC 0591-3196-89) tubes with a measured-dose applicator. Store at Controlled Room Temperature 15° - 30° C (59° - 86° F).

Terconazole Vaginal Cream 0.8% is available in 20 g (NDC 0591-3197-52) tubes with a measured-dose applicator. Store at Controlled Room Temperature 15° - 30° C (59° - 86° F).

Mfd. for:; Watson Laboratories, Inc. Corona, CA 92880 USA | Mfd. by:; Draxis Specialty Pharmaceuticals Inc. Kirkland, Quebec, Canada H9H 4J4 or
 | JOLLC Manati, Puerto Rico 00674
Printed in U.S.A. | Revised January 2010

PATIENT INFORMATION

TERCONAZOLE Vaginal Cream 0.4%
7–Day Regimen
TERCONAZOLE Vaginal Cream 0.8%
3–Day Regimen

PATIENT INSTRUCTIONS

Filling the Applicator:

1. Remove the cap from the tube.
2. Use the pointed tip on the top of the cap to puncture the seal on the tube.
3. Screw the applicator onto the tube.
4. Squeeze the tube from the bottom and fill the applicator until the plunger stops.
5. Unscrew the applicator from the tube.

Using the Applicator:

1. Lie on your back with your knees drawn up toward your chest.
2. Holding the applicator by the ribbed end of the barrel, insert the filled applicator into the vagina as far as it will comfortably go.
3. Slowly press the plunger of the applicator to release the cream into the vagina.
4. Remove the applicator from the vagina.
5. Apply one applicatorful each night for as many days at bedtime, as directed by your doctor.

Cleaning the Applicator:

After each use, you should thoroughly clean the applicator by following the procedure below:

1. Pull the plunger out of the barrel.
2. Wash the pieces with lukewarm, soapy water, and dry them thoroughly.
3. Put the applicator back together by gently pushing the plunger into the barrel as far as it will go.

NOTE: Store the cream at Controlled Room Temperature 15–30°C (59–86°F). See end flap for lot number and expiration date.

A WORD ABOUT YEAST INFECTIONS

Why Do Yeast Infections Occur?

Yeast infections are caused by an organism called Candida (KAN di duh). It may be present in small and harmless amounts in the mouth, digestive tract, and vagina. Sometimes the natural balance of the vagina becomes upset. This may lead to rapid growth of Candida, which results in a yeast infection. Symptoms of a yeast infection include itching, burning, redness, and an abnormal discharge.

Your doctor can make the diagnosis of a yeast infection by evaluating your symptoms and looking at a sample of the discharge under the microscope.

How Can I Prevent Yeast Infections?

Certain factors may increase your chance of developing a yeast infection. These factors don't actually cause the problem, but they may create a situation that allows the yeast to grow rapidly.

- Clothing: Tight jeans, nylon underwear, pantyhose, and wet bathing suits can hold in heat and moisture (two conditions in which yeast organisms thrive). Looser pants or skirts, 100% cotton underwear, and stockings may help avoid this problem.
- Diet: Cutting down on sweets, milk products, and artificial sweeteners may reduce the risk of yeast infections.
- Antibiotics: Antibiotics work by eliminating disease-causing organisms. While they are helpful in curing other problems, antibiotics may lead to an overgrowth of Candida in the vagina.
- Pregnancy: Hormonal changes in the body during pregnancy encourage the growth of yeast. This is a very common time for an infection to occur. Until the baby is born, it may be hard to completely eliminate yeast infections. If you believe you are pregnant, tell your doctor.
- Menstruation: Sometimes monthly changes in hormone levels may lead to yeast infections.
- Diabetes: In addition to heat and moisture, yeast thrives on sugar. Because diabetics often have sugar in their urine, their vaginas are rich in this substance. Careful control of diabetes may help prevent yeast infection.

Controlling these factors can help eliminate yeast infections and may prevent them from coming back.

Some Other Helpful Tips:

1. For best results, be sure to use the medication as prescribed by your doctor, even if you feel better quickly.
2. Avoid sexual intercourse, if your doctor advises you to do so.
3. If your partner has any penile itching, redness, or discomfort, he should consult his physician and mention that you are being treated for a yeast infection.
4. You can use the medication even if you are having your menstrual period. However, you should not use tampons because they may absorb the medication. Instead, use external pads or napkins until you have finished your medication. You may also wish to wear a sanitary napkin if the vaginal medication leaks.
5. Dry the genital area thoroughly after showering, bathing, or swimming. Change out of a wet bathing suit or damp exercise clothes as soon as possible. A dry environment is less likely to encourage the growth of yeast.
6. Wipe from front to rear (away from the vagina) after a bowel movement.
7. Don't douche unless your doctor specifically tells you to do so. Douching may disturb the vaginal balance.
8. Don't scratch if you can help it. Scratching can cause more irritation and spread the infection.
9. Discuss with your physician any medication you are already taking. Certain types of medication can make your vagina more susceptible to infection.
10. Eat nutritious meals to promote your general health.

Mfd. for:; Watson Laboratories, Inc. Corona, CA 92880 USA | Mfd. by:; Draxis Specialty Pharmaceuticals Inc. Kirkland, Quebec, Canada H9H 4J4 or
 | JOLLC Manati, Puerto Rico 00674
Printed in U.S.A. | Revised January 2010

PRINCIPAL DISPLAY PANEL

NDC 55045-3259-03

PRINCIPAL DISPLAY PANEL

Terconazole Vaginal Cream
0.8%
Tube and Applicator
For Vaginal Use Only.

Rx only

Net Wt 0.71 oz. (20 g)
Quantity by weight not by volume.